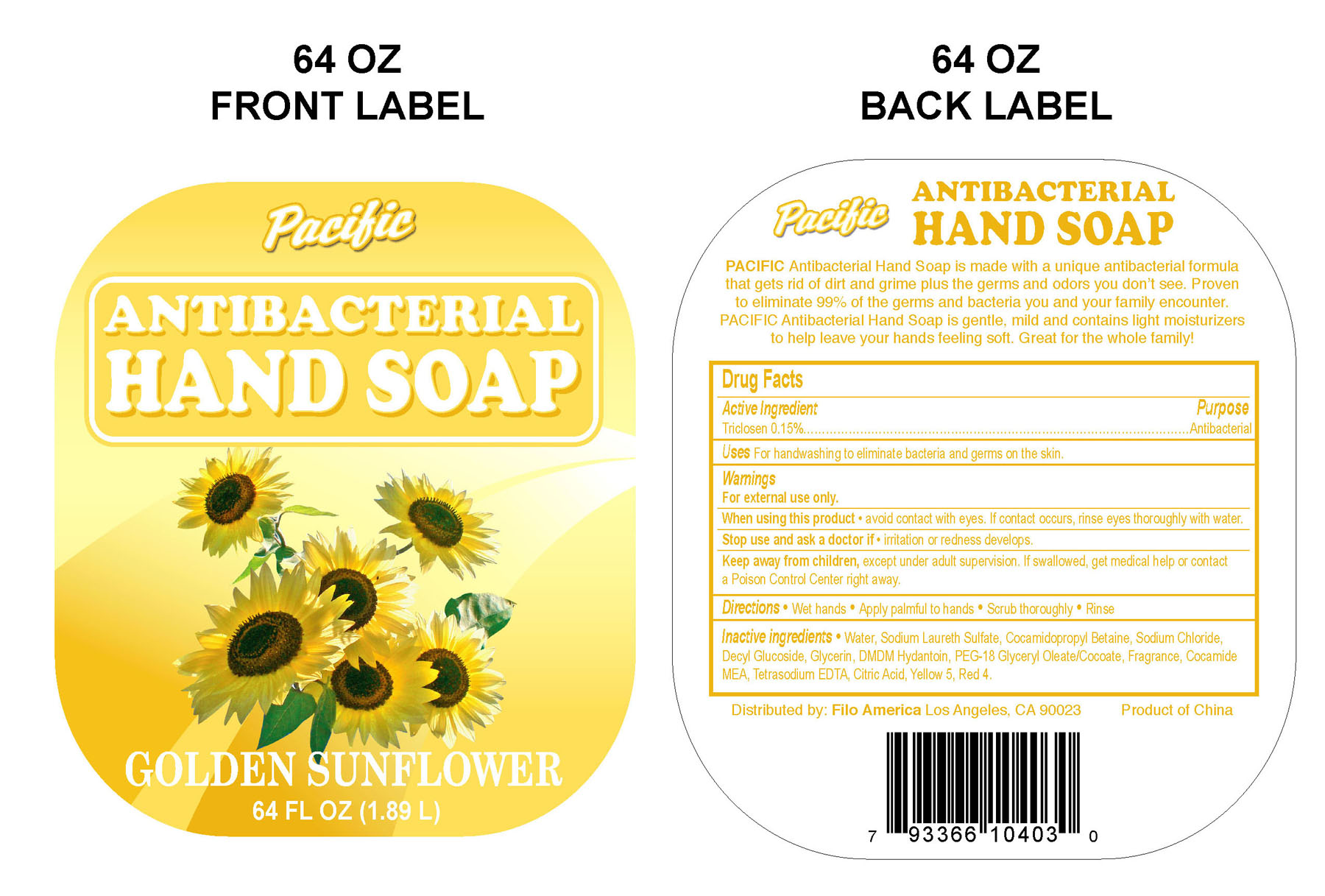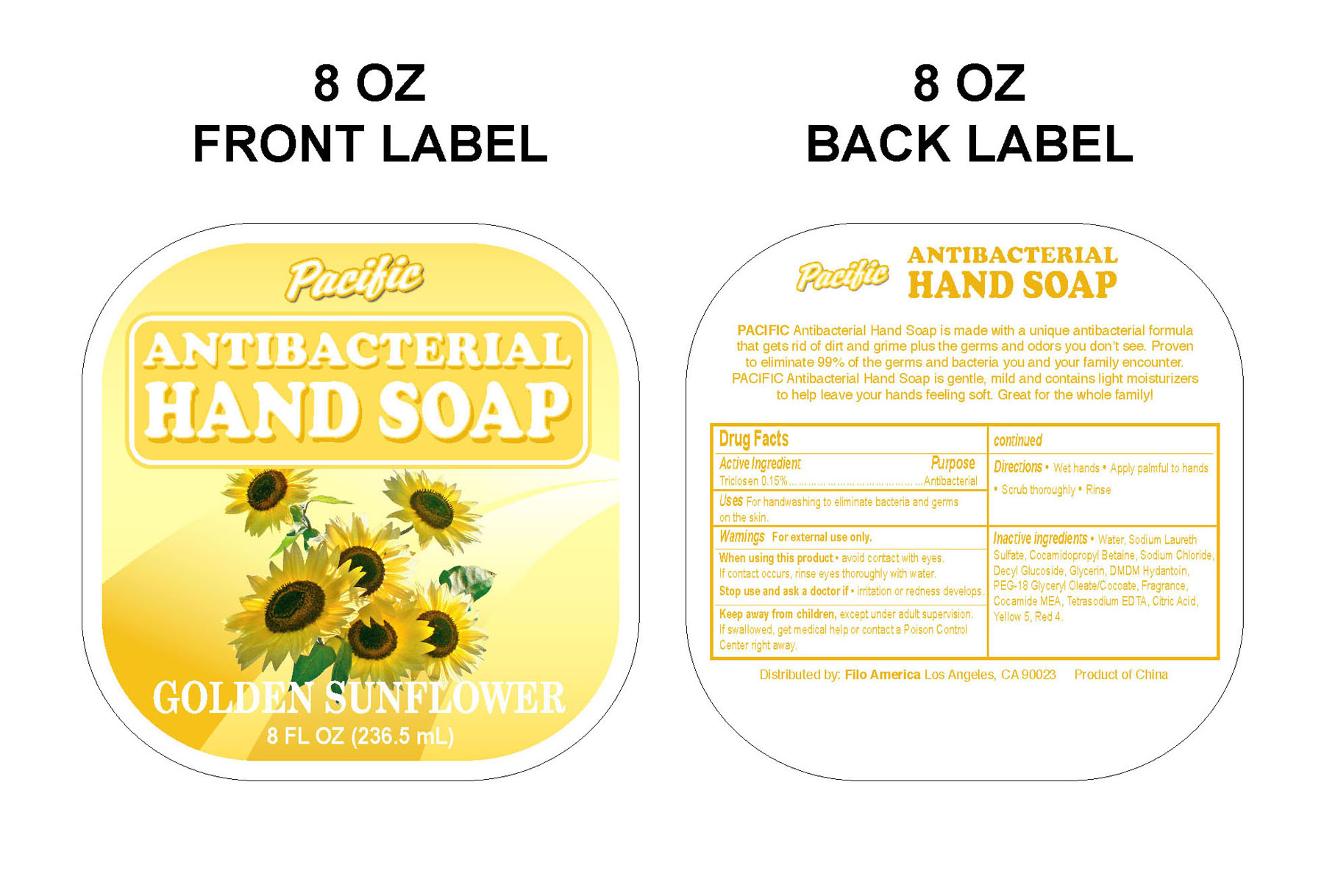 DRUG LABEL: Pacific 
NDC: 29860-221 | Form: SOAP
Manufacturer: Ningbo United
Category: otc | Type: HUMAN OTC DRUG LABEL
Date: 20100304

ACTIVE INGREDIENTS: TRICLOSAN 318.975 mL/2126.5 mL
INACTIVE INGREDIENTS: Water; Sodium Laureth Sulfate; Cocamidopropyl Betaine; Sodium Chloride; Glycerin; GLYCERYL MONOOLEATE; CITRIC ACID MONOHYDRATE

Pacific Antibacterial Hand Soap Drug Facts

ACTIVE INGREDIENT

Triclosan 0.15%......................................................................Antibacterial

PURPOSE

Uses For handwashing to eliminate bacteria and germs on the skin.

WARNINGS

For external use only.

WHEN USING

Avoid contact with eyes. If contact occurs, rinse eyes thoroughly with water.

Stop use and ask a doctor if irritation or redness develops.

KEEP OUT OF REACH OF CHILDREN

Keep away from children, except under adult supervision. If swallowed, get medical help or contact a Poison Control Center right away.

INDICATIONS AND USAGE

Directions * Wet Hands * Apply palmful to hands * Scrub thoroughly * Rinse

INACTIVE INGREDIENT

Water, Sodium Laureth Sulfate, Cocamidopropyl Betaine, Sodium Chloride, Decyl Glucoside, Glycerin, DMDM Hydantoin, PEG-18 Glyceryl Oleate/Cocoate, Fragrance, Cocamide MEA, Tetrasodium EDTA, Citric Acid, FD and C Yellow No. 5.

PACKAGE LABEL

MM1
MM2